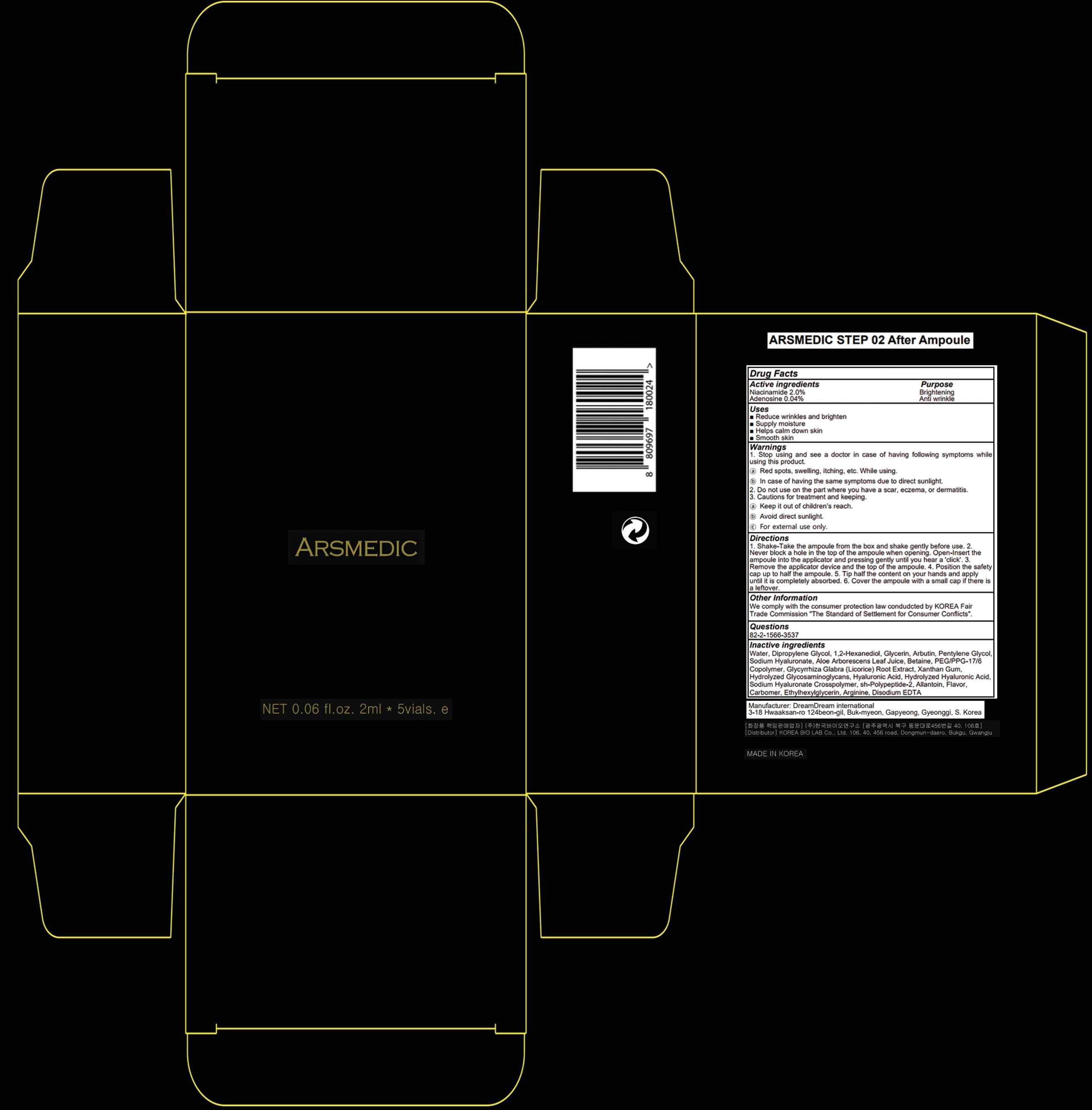 DRUG LABEL: ARSMEDIC STEP 02 After Ampoule
NDC: 82267-020 | Form: LIQUID
Manufacturer: Korea Bio Lab Co., Ltd
Category: otc | Type: HUMAN OTC DRUG LABEL
Date: 20210924

ACTIVE INGREDIENTS: Niacinamide 2.0 g/100 mL; Adenosine 0.04 g/100 mL
INACTIVE INGREDIENTS: Water; Dipropylene Glycol; 1,2-Hexanediol

ACTIVE INGREDIENTS

Niacinamide 2.0%
Adenosine 0.04%

PURPOSE

Brightening
Anti wrinkle

Uses

■ Reduce wrinkles and brighten
■ Supply moisture
■ Helps calm down skin
■ Smooth skin

WARNINGS

1. Stop using and see a doctor in case of having following symptoms while using this product.
ⓐ Red spots, swelling, itching, etc. While using.
ⓑ In case of having the same symptoms due to direct sunlight.
2. Do not use on the part where you have a scar, eczema, or dermatitis.
3. Cautions for treatment and keeping.
ⓐ Keep it out of children’s reach.
ⓑ Avoid direct sunlight.
ⓒ For external use only.

KEEP OUT OF REACH OF CHILDREN

Keep it out of children’s reach.

Directions

1. Shake-Take the ampoule from the box and shake gently before use. 2. Never block a hole in the top of the ampoule when opening. Open-Insert the ampoule into the applicator and pressing gently until you hear a 'click'. 3. Remove the applicator device and the top of the ampoule. 4. Position the safety cap up to half the ampoule. 5. Tip half the content on your hands and apply until it is completely absorbed. 6. Cover the ampoule with a small cap if there is a leftover.

Other Information

We comply with the consumer protection law condudcted by KOREA Fair Trade Commission "The Standard of Settlement for Consumer Conflicts".

QUESTIONS

82-2-1566-3537

INACTIVE INGREDIENTS

Water, Dipropylene Glycol, 1,2-Hexanediol, Glycerin, Arbutin, Pentylene Glycol, Sodium Hyaluronate, Aloe Arborescens Leaf Juice, Betaine, PEG/PPG-17/6 Copolymer, Glycyrrhiza Glabra (Licorice) Root Extract, Xanthan Gum, Hydrolyzed Glycosaminoglycans, Hyaluronic Acid, Hydrolyzed Hyaluronic Acid, Sodium Hyaluronate Crosspolymer, sh-Polypeptide-2, Allantoin, Flavor, Carbomer, Ethylhexylglycerin, Arginine, Disodium EDTA